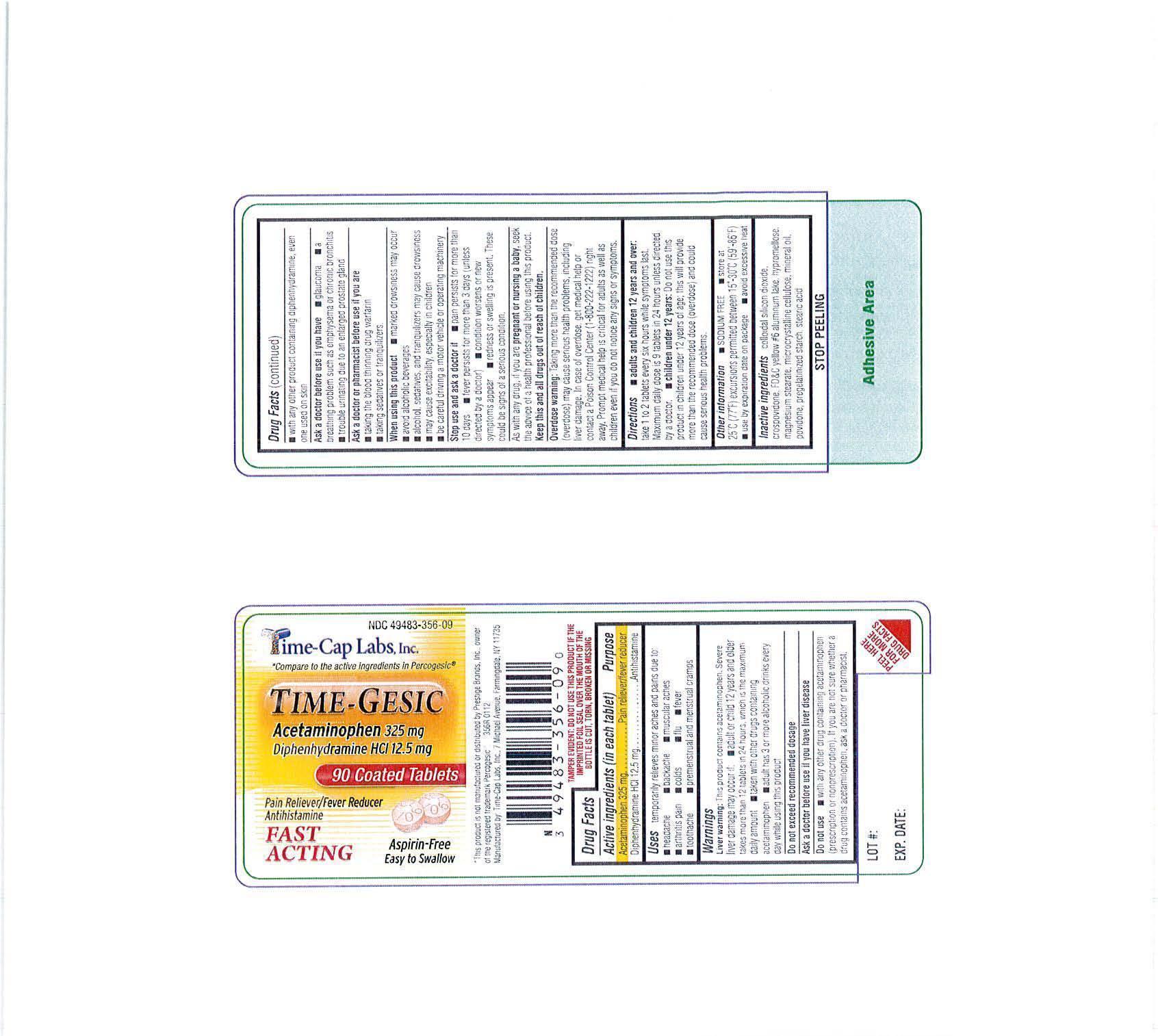 DRUG LABEL: TIME-GESIC
NDC: 49483-356 | Form: TABLET, COATED
Manufacturer: Time-Cap Labs, Inc
Category: otc | Type: HUMAN OTC DRUG LABEL
Date: 20191122

ACTIVE INGREDIENTS: ACETAMINOPHEN 325 mg/1 1; DIPHENHYDRAMINE HYDROCHLORIDE 12.5 mg/1 1
INACTIVE INGREDIENTS: SILICON DIOXIDE; CROSPOVIDONE; FD&C YELLOW NO. 6; HYPROMELLOSES; MAGNESIUM STEARATE; CELLULOSE, MICROCRYSTALLINE; POVIDONE; STARCH, PREGELATINIZED CORN; STEARIC ACID

356R APAP/DIPHEN hcl tABS 325/12.5 ORANGE FC CLEAR

Do not use

- WITH ANY OTHER DRUG CONTAINING ACETAMINOPHEN(PRESCRIPTION OR NONPRESCRIPTION). IF YOU ARE NOT SURE WHETHER A DRUG CONTAINS ACETAMINOPHEN, ASK A DOCTOR OR PHARMACIST.

Ask a doctor before use if you have liver disease.

Ask a doctor or pharmacist before use if you are

- taking the blood thinning drug warfarin
- taking sedatives or tranquilizers

Stop use and ask a doctor if

pain persists for more than 10 days; fever persists for more than 3 days (unless directed by a doctor); condition worsens or new symptoms appear; redness or swelling is present. These could be signs of a serious condition.

PREGNANCY OR BREAST FEEDING

If pregnant or nursing, as with any drug, seek the advise of a health professional before using this product.

KEEP OUT OF REACH OF CHILDREN

Keep this and all drugs out of reach of children.

Directions
adults and children 12 years and over: take 1 to 2 tablets every six hours while symptoms last. Maximum daily dose is 9 tablets in 24 hours unless directed by a doctor.

children under 12 years: Do not use this product in children under 12 years of age; this will provide more than the recommended dose (overdose) and could cause serious health problems.

Other information

- store at 25° C (77° F) excursions permitted between 15°-30° C (59°-86° F)
- use by expiration date on package
- avoid excessive heat
- sodium free

INACTIVE INGREDIENT

colloidal silicon dioxide, crospovidone, fd&C yellow #6 aluminum lake, hypromellose, magnesium stearate, microcrystalline cellulose, mineral oil, povidone, pregelatinized starch, stearic acid

INDICATIONS AND USAGE

Uses: temporarily releives mnor aches and pains due to:

headache, backache, muscular aches, arthritis pain, colds, flu, fever, toothache, premenstrual cramps.

PURPOSE

Pain Reliever-fever reducer-antihistamine

Warnings:

Liver warning: This product contains acetaminophen. Severe liver damage may occur if: adult or child 12 years and older takes more than 12 tablets in 24 hours, which is the maximum daily amount; taking with other durgs containing acetaminophen; adult has 3 or more alcoholic drinks every day while using this product.

ACTIVE INGREDIENT

Each tablet contains:

acetaminophen 325 mg

diphenhydramine HCl 12.5 mg